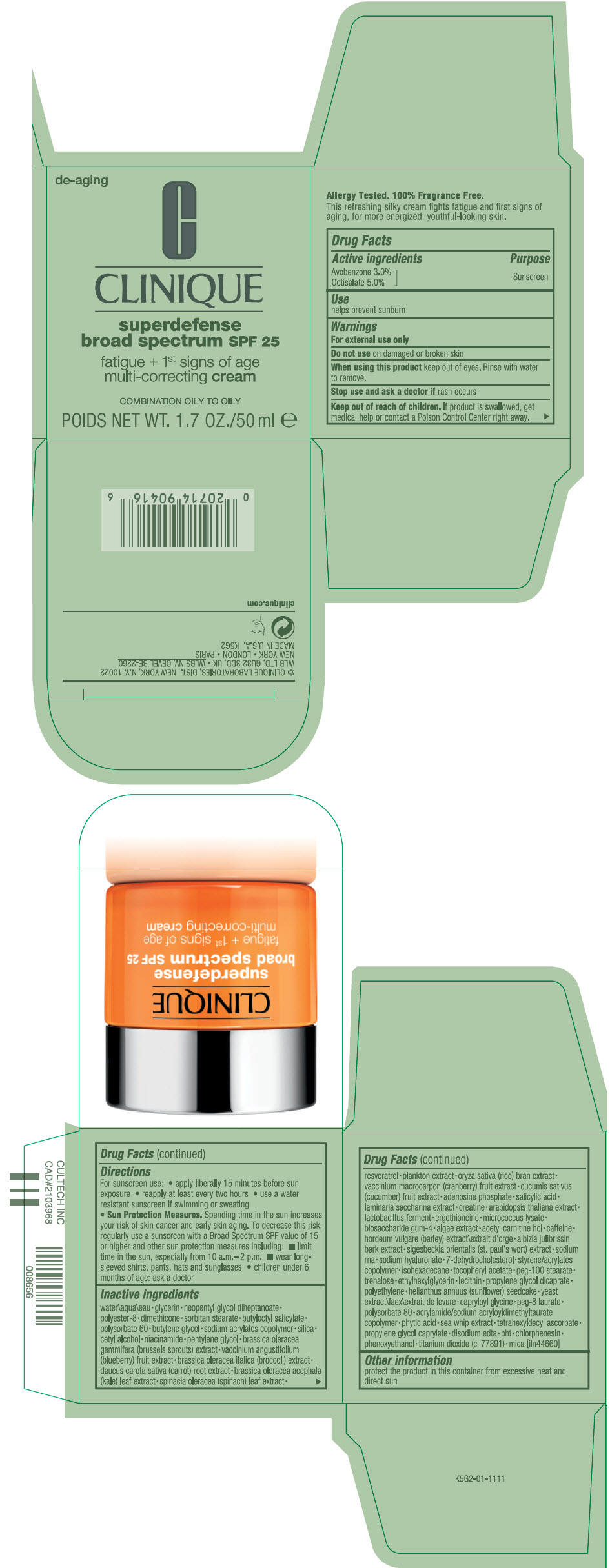 DRUG LABEL: SUPERDEFENSE BROAD SPECTRUM SPF 25 FATIGUE plus 1ST SIGNS OF AGE MULTI-CORRECTING
NDC: 49527-075 | Form: CREAM
Manufacturer: CLINIQUE LABORATORIES LLC
Category: otc | Type: HUMAN OTC DRUG LABEL
Date: 20241225

ACTIVE INGREDIENTS: AVOBENZONE 0.0306 g/1 mL; OCTISALATE 0.051 g/1 mL
INACTIVE INGREDIENTS: GLYCERIN; NEOPENTYL GLYCOL DIHEPTANOATE; POLYESTER-8 (1400 MW, CYANODIPHENYLPROPENOYL CAPPED); DIMETHICONE; SORBITAN MONOSTEARATE; BUTYLOCTYL SALICYLATE; POLYSORBATE 60; BUTYLENE GLYCOL; SILICON DIOXIDE; CETYL ALCOHOL; NIACINAMIDE; PENTYLENE GLYCOL; BRUSSELS SPROUT; LOWBUSH BLUEBERRY; BROCCOLI; CARROT; KALE; SPINACH; RESVERATROL; RICE BRAN; CRANBERRY; CUCUMBER; ADENOSINE PHOSPHATE; SALICYLIC ACID; SACCHARINA LATISSIMA; CREATINE; ARABIDOPSIS THALIANA WHOLE; LIMOSILACTOBACILLUS REUTERI; ERGOTHIONEINE; BIOSACCHARIDE GUM-4; LEVACECARNINE HYDROCHLORIDE; CAFFEINE; BARLEY; ALBIZIA JULIBRISSIN BARK; HYALURONATE SODIUM; 7-DEHYDROCHOLESTEROL; ISOHEXADECANE; .ALPHA.-TOCOPHEROL ACETATE; PEG-100 STEARATE; TREHALOSE; ETHYLHEXYLGLYCERIN; PROPYLENE GLYCOL DICAPRATE; HIGH DENSITY POLYETHYLENE; HELIANTHUS ANNUUS SEEDCAKE; YEAST, UNSPECIFIED; CAPRYLOYL GLYCINE; PEG-8 LAURATE; POLYSORBATE 80; FYTIC ACID; PSEUDOPTEROGORGIA ELISABETHAE; TETRAHEXYLDECYL ASCORBATE; PROPYLENE GLYCOL MONOCAPRYLATE; EDETATE DISODIUM ANHYDROUS; BUTYLATED HYDROXYTOLUENE; CHLORPHENESIN; PHENOXYETHANOL; TITANIUM DIOXIDE; MICA; WATER

SUPERDEFENSE BROAD SPECTRUM SPF 25 FATIGUE + 1ST SIGNS OF AGE MULTI-CORRECTING CREAM

Drug Facts

Active ingredients

Avobenzone 3.0%
Octisalate 5.0%

Purpose

Sunscreen

Use

helps prevent sunburn

Warnings

For external use only

Do not use on damaged or broken skin

When using this product keep out of eyes. Rinse with water to remove.

Stop use and ask a doctor if rash occurs

Keep out of reach of children. If product is swallowed, get medical help or contact a Poison Control Center right away.

Directions

For sunscreen use:

- apply liberally 15 minutes before sun exposure
- reapply at least every two hours
- use a water resistant sunscreen if swimming or sweating
- Sun Protection Measures. Spending time in the sun increases your risk of skin cancer and early skin aging. To decrease this risk, regularly use a sunscreen with a Broad Spectrum SPF value of 15 or higher and other sun protection measures including:
  - limit time in the sun, especially from 10 a.m.–2 p.m.
  - wear long-sleeved shirts, pants, hats and sunglasses
- children under 6 months of age: ask a doctor

Inactive ingredients

water\aqua\eau • glycerin • neopentyl glycol diheptanoate • polyester-8 • dimethicone • sorbitan stearate • butyloctyl salicylate • polysorbate 60 • butylene glycol • sodium acrylates copolymer • silica • cetyl alcohol • niacinamide • pentylene glycol • brassica oleracea gemmifera (brussels sprouts) extract • vaccinium angustifolium (blueberry) fruit extract • brassica oleracea italica (broccoli) extract • daucus carota sativa (carrot) root extract • brassica oleracea acephala (kale) leaf extract • spinacia oleracea (spinach) leaf extract • resveratrol • plankton extract • oryza sativa (rice) bran extract • vaccinium macrocarpon (cranberry) fruit extract • cucumis sativus (cucumber) fruit extract • adenosine phosphate • salicylic acid • laminaria saccharina extract • creatine • arabidopsis thaliana extract • lactobacillus ferment • ergothioneine • micrococcus lysate • biosaccharide gum-4 • algae extract • acetyl carnitine hcl • caffeine • hordeum vulgare (barley) extract\extrait d'orge • albizia julibrissin bark extract • sigesbeckia orientalis (st. paul's wort) extract • sodium rna • sodium hyaluronate • 7-dehydrocholesterol • styrene/acrylates copolymer • isohexadecane • tocopheryl acetate • peg-100 stearate • trehalose • ethylhexylglycerin • lecithin • propylene glycol dicaprate • polyethylene • helianthus annuus (sunflower) seedcake • yeast extract\faex\extrait de levure • capryloyl glycine • peg-8 laurate • polysorbate 80 • acrylamide/sodium acryloyldimethyltaurate copolymer • phytic acid • sea whip extract • tetrahexyldecyl ascorbate • propylene glycol caprylate • disodium edta • bht • chlorphenesin • phenoxyethanol • titanium dioxide (ci 77891) • mica [iln44660]

Other information

protect the product in this container from excessive heat and direct sun

PRINCIPAL DISPLAY PANEL - 50 ml Jar Carton

de-aging

CLINIQUE

superdefense
broad spectrum SPF 25

fatigue + 1st signs of age
multi-correcting cream

COMBINATION OILY TO OILY

NET WT. 1.7 OZ./50 ml e